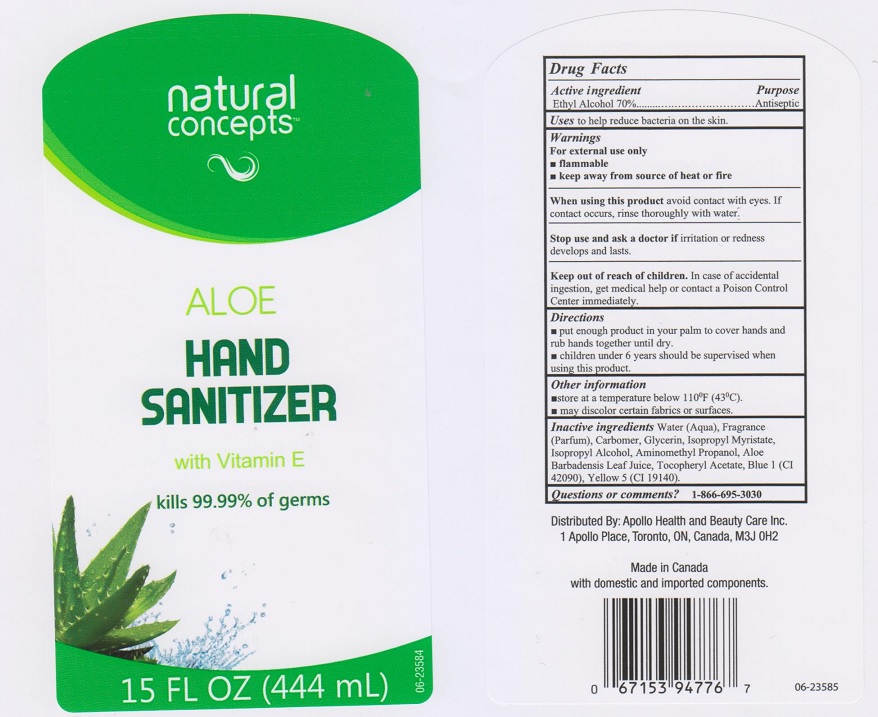 DRUG LABEL: Natural Concepts Aloe Hand Sanitizer
NDC: 63148-508 | Form: GEL
Manufacturer: Apollo Health and Beauty Care Inc.
Category: otc | Type: HUMAN OTC DRUG LABEL
Date: 20190124

ACTIVE INGREDIENTS: ALCOHOL 700 mg/1 mL
INACTIVE INGREDIENTS: WATER; CARBOMER 934; GLYCERIN; ISOPROPYL MYRISTATE; ISOPROPYL ALCOHOL; AMINOMETHYLPROPANOL; ALOE VERA LEAF; .ALPHA.-TOCOPHEROL ACETATE, DL-; FD&C BLUE NO. 1; FD&C YELLOW NO. 5

Drug Facts

Active ingredient

Ethyl Alcohol 70%

Purpose

Antiseptic

Uses

to help reduce bacteria on the skin.

Warnings

For external use only

- flammable
- keep away from source of heat or fire

When using this product

avoid contact with eyes. If contact occurs, rinse thoroughly with water.

Stop use and ask a doctor if

irritation or redness develops and lasts.

Keep out of reach of children.

In case of accidental ingestion, get medical help or contact a Poison Control Center immediately

Directions

- put enough product in your palm to cover hands and rub hands together until dry.
- children under 6 years should be supervised when using this product.

Other information

- store at a temperature below 110°F (43°C).
- may discolor certain fabrics or surfaces.

Inactive ingredients

Water (Aqua), Fragrance (Parfum), Carbomer, Glycerin, Isopropyl Myristate, Isopropyl Alcohol, Aminomethyl Propanol, Aloe Barbadensis Leaf Juice, Tocopheryl Acetate, Blue 1 (CI 42090), Yellow 5 (CI 19140).

Questions or comments?

1-866-695-3030